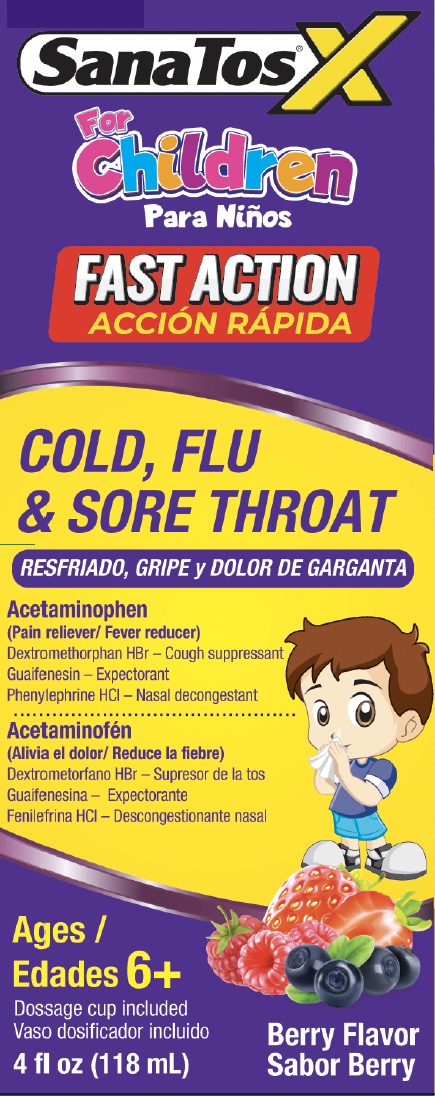 DRUG LABEL: SanaTos X Children
NDC: 55758-443 | Form: LIQUID
Manufacturer: Pharmadel LLC
Category: otc | Type: HUMAN OTC DRUG LABEL
Date: 20240815

ACTIVE INGREDIENTS: ACETAMINOPHEN 325 mg/10 mL; DEXTROMETHORPHAN HYDROBROMIDE 10 mg/10 mL; GUAIFENESIN 200 mg/10 mL; PHENYLEPHRINE HYDROCHLORIDE 5 mg/10 mL
INACTIVE INGREDIENTS: PROPYLENE GLYCOL; SUCRALOSE; SODIUM BENZOATE; XANTHAN GUM; PROPYL GALLATE; WATER; SORBITOL; ANHYDROUS CITRIC ACID; FD&C BLUE NO. 1; FD&C RED NO. 40; GLYCERIN; EDETATE DISODIUM

SanaTos X Children (Apta)

Active ingredients & Purposes

Active ingredient (in each 10 mL) | Purposes
Acetaminophen 325 mg ..................................... | Pain reliever/ fever reducer
Dextromethorphan HBr 10 mg............................... | Cough suppressant
Guaifenesin 200 mg............................................... | Expectorant
Phenylephrine HCI 5 mg........................................ | Nasal decongestant

Uses

- temporarily relieves these common cold/ flu symptoms:
- nasal congestion
- headache
- sore throat
- minor aches and pains
- cough due to minor throat and bronchial irritation
- temporarily reduces fever
- helps loosen phlegm (mucus) and thin bronchial secretions to drain bronchial tubes

Warnings

Liver warning: This product contains acetaminophen. Severe liver damage may occur if your child takes

- more than 5 doses in 24 hours, which is the maximum daily amount
- with other drugs containing acetaminophen

Allergy alert: Acetaminophen may cause severe skin reactions. Symptoms may include:

- skin reddening
- blisters
- rash

If a skin reaction occurs, stop use and seek medical help right away.

Sore throat warning: If sore throat is severe, persists for more than 2 days, is accompanied or followed by fever, headache, nausea, and vomiting, consult doctor promptly

Do not use

- with any other drug containing acetaminophen (prescription or nonprescription). If you are not sure whether a drug contains acetaminophen, ask a doctor or pharmacist.
- in a child who is taking a prescription monoamine oxidase inhibitor (MAOI) (certain drugs for depression, psychiatric, or emotional conditions, or Parkinson's disease), or for 2 weeks after stopping the MAOI drug. If you do not know if your child’s prescription drug contains an MAOI, ask a doctor or pharmacist before taking product.

Ask a doctor or pharmacist before use if your child is

aking the blood thinning drug warfarin.

Ask a doctor before use if your child has

- liver disease
- a cough that is accompanied with excessive phlegm (mucus)
- a persistent or chronic cough such as occurs with asthma
- heart disease
- high blood pressure
- thyroid disease
- diabetes

When using this product do not exceed recommended dosage.

- do not use more than directed

Stop use and ask a doctor if

- pain, cough, or nasal congestion gets worse or lasts more than 5 days
- fever gets worse or lasts more than 3 days
- redness or swelling is present
- new symptoms occur
- nervousness, dizziness, or sleeplessness occur

Keep out of reach of children.

Overdose warning: Taking more than the recommended dose (overdose) may cause liver damage. In case of overdose, get medical help or contact a Poison Control Center right away. Prompt medical attention is critical even if you do not notice any signs or symptoms.

Directions

- this product does not contain directions or complete warnings for adult use
- do not give more than directed (see Overdose warning)
- shake well before use
- children 6 to under 12 years of age: take 10 mL in dosing cup provided every 4 hours, while symptoms persist, up to 5 times a day or as directed by a doctor
- children under 6 years of age: do not use

Other information

- each 10 mL contains: sodium 5 mg
- store between 59-86°F (15-30°C)
- do not refrigerate

Inactive ingredients

anhydrous citric acid, edetate disodium, FD&C blue no. 1, FD&C red no. 40, flavors, glycerin, propylene glycol, propyl gallate, purified water, sodium benzoate, sorbitol, sucralose, xanthan gum

Questions

+1-866-359-3478 (M-F) 9 AM to 5 PM EST or www.pharmadel.com